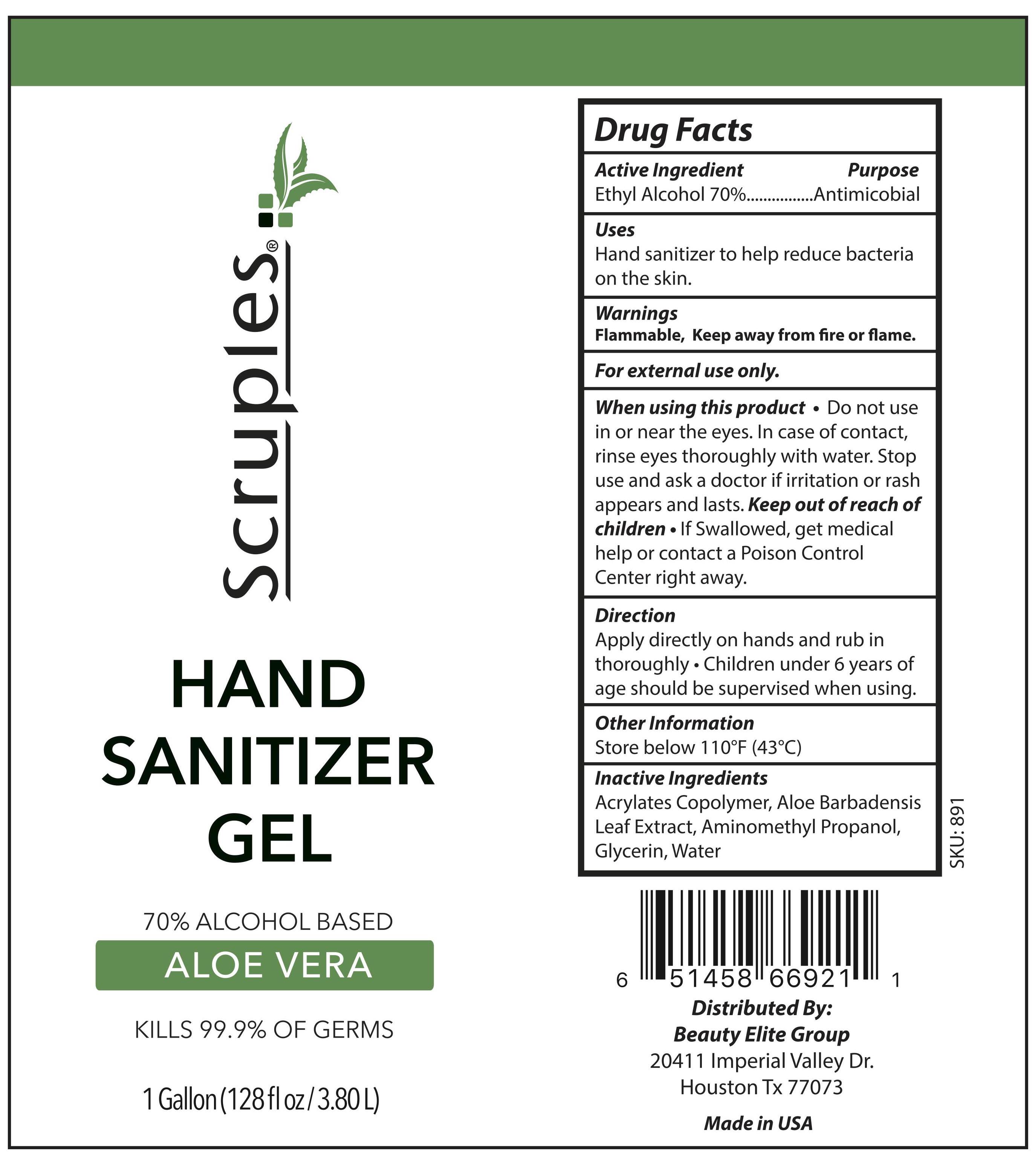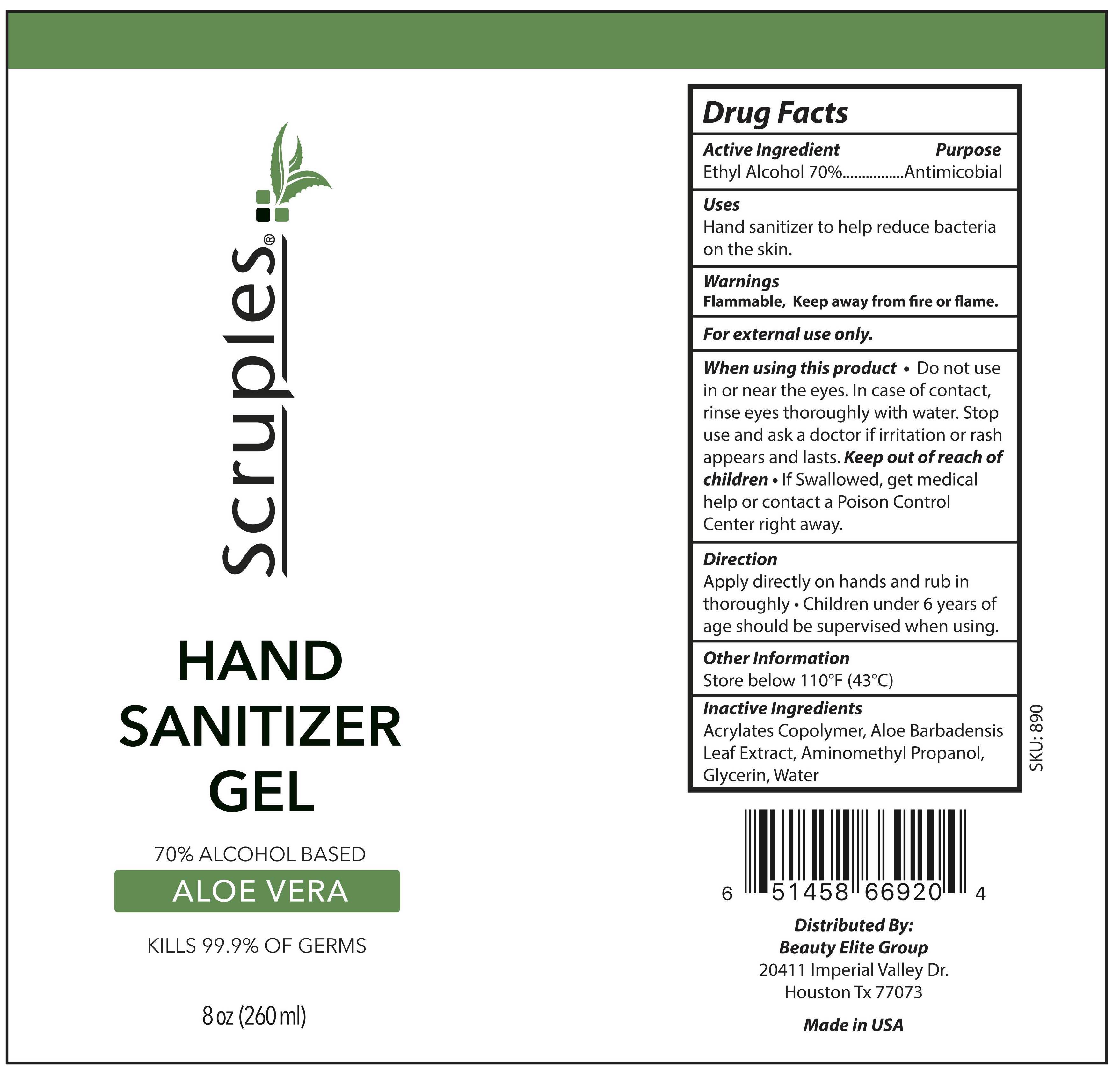 DRUG LABEL: Hand Sanitizer
NDC: 77664-920 | Form: GEL
Manufacturer: Beauty Elite Group
Category: otc | Type: HUMAN OTC DRUG LABEL
Date: 20200511

ACTIVE INGREDIENTS: ALCOHOL 70 mL/100 mL
INACTIVE INGREDIENTS: GLYCERIN 1.45 mL/100 mL; WATER

Hand Sanitizer Gel

Active Ingredient(s)

Alcohol 70% v/v. Purpose: Antimicrobial

Purpose

Antimicrobial, Hand Sanitizer

Use

Hand sanitizer to help reduce bacteria on the skin.

Warnings

For external use only. Flammable. Keep away from fire or flame

When using this product do not use in or near the eyes. In case of contact, rinse eyes thoroughly with water.

Stop use and ask a doctor if irritation or rash appears and lasts.

Keep out of reach of children. If Swallowed, get medical help or contact a Poison Control Center right away.

Stop use and ask a doctor if irritation or rash occurs. These may be signs of a serious condition.

Keep out of reach of children. If swallowed, get medical help or contact a Poison Control Center right away.

Directions

- Apply directly on hands and rub in thoroughly
- Children under 6 years of age should be supervised when using.

Other information

- Store below 110°F (43°C)

Inactive ingredients

Acrylates Copolymer, Aloe Barbadensis Leaf Extract, Aminomethyl Propanol, Glycerin, Water

Package Label - Principal Display Panel

236 mL NDC: 77664-920-01

3785 mL NDC: 77664-920-02